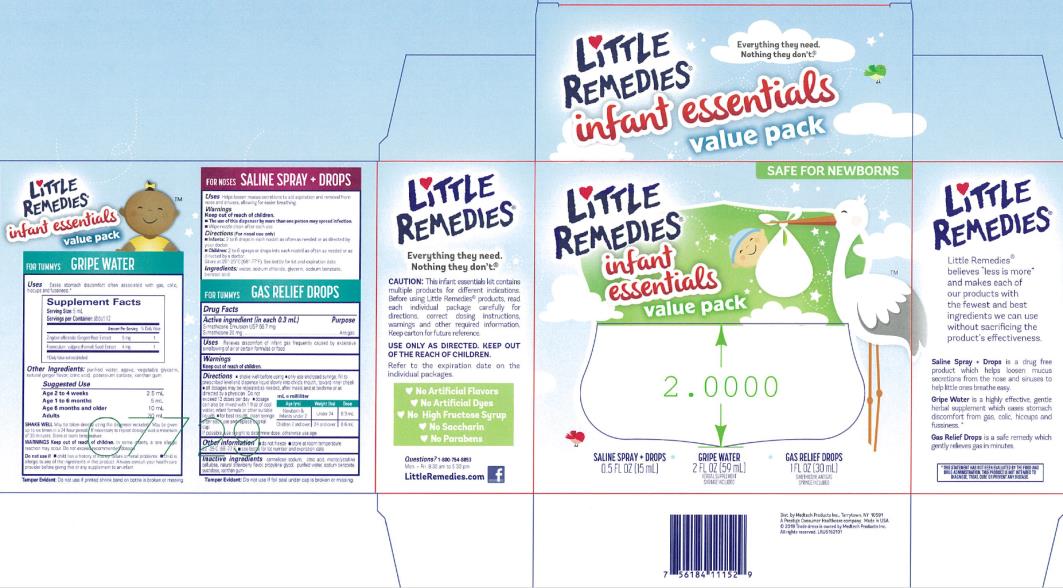 DRUG LABEL: LITTLE REMEDIES INFANT ESSENTIALS
NDC: 63029-609 | Form: KIT | Route: ORAL
Manufacturer: Medtech Products Inc.
Category: otc | Type: HUMAN OTC DRUG LABEL
Date: 20200101

ACTIVE INGREDIENTS: DIMETHICONE 20 mg/0.3 mL; GINGER 5 mg/5 mL; FENNEL 4 mg/5 mL
INACTIVE INGREDIENTS: CARBOXYMETHYLCELLULOSE SODIUM; CITRIC ACID MONOHYDRATE; CELLULOSE, MICROCRYSTALLINE; PROPYLENE GLYCOL; WATER; SODIUM BENZOATE; SUCROSE; XANTHAN GUM; CITRIC ACID MONOHYDRATE; AGAVE TEQUILANA JUICE; WATER; GLYCERIN; POTASSIUM SORBATE; XANTHAN GUM

Little Remedies Infant Essentials Kit

GAS RELIEF DROPS Simethicone / Antigas

Drug Facts

Purpose

Simethicone Emulsion USP 66.7 mg/ Simethicone 20 mg . . . . . . . . . . . . . . . ……..Antigas

Uses

Relieves discomfort of infant gas frequently caused by excessive swallowing of air or certain formulas or food

Directions

■ shake well before using

■ only use enclosed syringe; fill to prescribed level and dispense liquid slowly into child’s mouth, toward inner cheek

■ all dosages may be repeated as needed, after meals and at bedtime or as directed by a physician. Do not exceed 12 doses per day.

■ dosage can also be mixed with 1 oz. of cool water, infant formula or other suitable liquids

■ for best results, clean syringe after each use and replace original cap

If possible, use weight to determine dose; otherwise use age.

mL = milliliters

Age (yrs) | Weight (lbs) | Dose
Newborns & Infants under 2 years | under 24 | 0.3 mL
Children 2 years and over | 24 and over | 0.6 mL

Other information

■ do not freeze ■ store at room temperature 20˚-25˚C (68˚-77˚F)

■ See bottle or box for lot number and expiration date

Inactive ingredients

carmellose sodium,citric acid, microcrystalline cellulose, natural strawberry flavor, propylene glycol, purified water, sodium benzoate, sucralose, xanthan gum

GRIPE WATER

Supplement Facts
Serving Size: 5 mL
Servings per Container: about 12
Amount per Serving | % Daily Value
Zingiber officinale (Ginger) Root Extract 5 mg | †
Foeniculum vulgare (Fennel) Seed Extract 4mg | †
†Daily Value not established

Other ingredients

purified water, agave, glycerin, natural ginger flavor, potassium sorbate, citric acid, xanthan gum

Suggested Use
Age | Dose
2 to 4 weeks | 2.5 mL
1 to 6 months | 5 mL
6 months and older | 10 mL
Adults | 30 mL

SHAKE WELL. May be taken directly using the dispenser included. May be given up to six times in a 24 hour period. If necessary to repeat dosage, wait a minimum of 30 minutes. Do not use if safety seal is broken or missing.

Keep out of reach of children.

In some infants, a rare allergic reaction may occur. Do not exceed recommended dosage.

Do not use if

- child has a history of kidney failure or renal problems
- child is allergic to any of the ingredients in this product Always consult your health care provider before giving this or any supplement to an infant.
- Store at room temperature.

SALINE SPRAY + DROPS

Uses

–Helps loosen mucus secretions to aid aspiration and removal from nose and sinuses, allowing for easier breathing. For infants this can be assisted with the use of our specially designed “Soft Tip” Nasal Aspirator.

Warnings

Keep out of reach of children.

▪ The use of this dispenser by more than one person may spread infection.

▪ Wipe nozzle clean after each use.

Directions (For nasal use only)

▪ Infants: 2 to 6 drops in each nostril as often as needed or as directed by your doctor.

▪Children: 2 to 6 sprays or drops into each nostril as often as needed or as directed by a doctor.

Store at 20°-25°C (68°-77°F).

See bottle for lot and expiration date.

Ingredients:

water, sodium chloride, glycerin, sodium benzoate, benzoic acid

PRINCIPAL DISPLAY PANEL

Little Remedies®

Infant Essentials Kit

GAS DROPS

SIMETHICONE /ANTIGAS

1 FL OZ (30 mL)

Syringe Included

SALINE SPRAY + DROPS

0.5 FL OZ (15 mL)

GRIPE WATER

GINGER / FENNEL SUPPLEMENT

2 FL OZ (59 mL)

Syringe Included